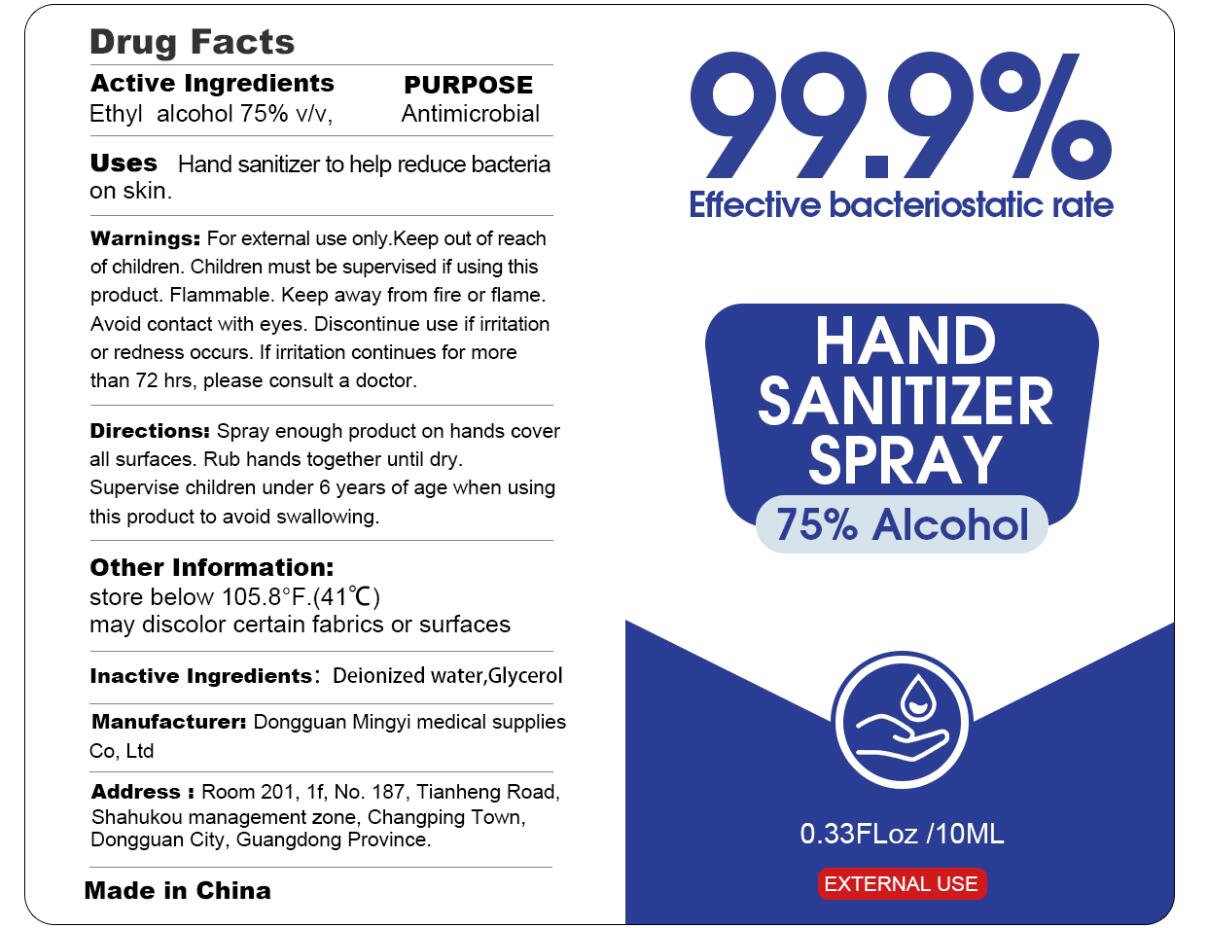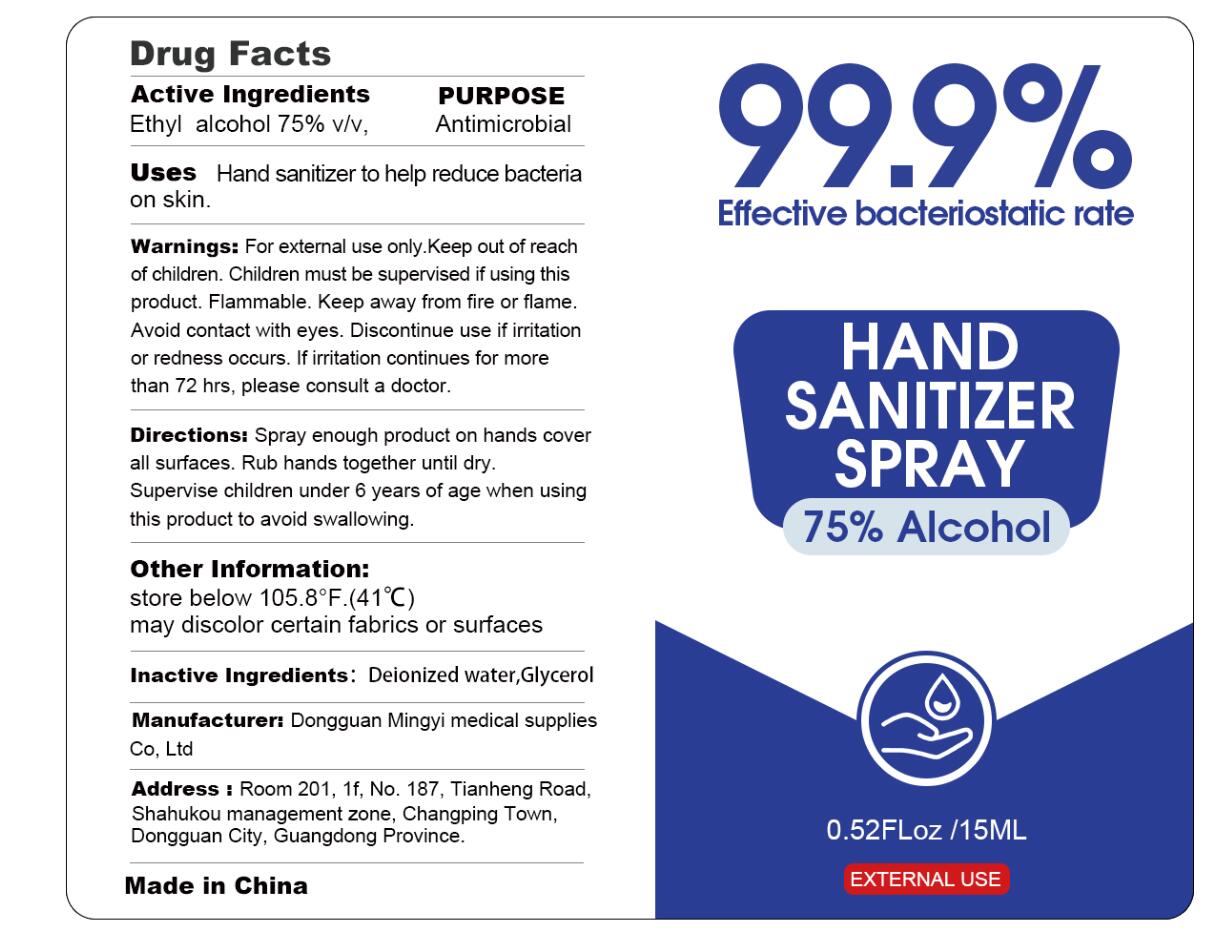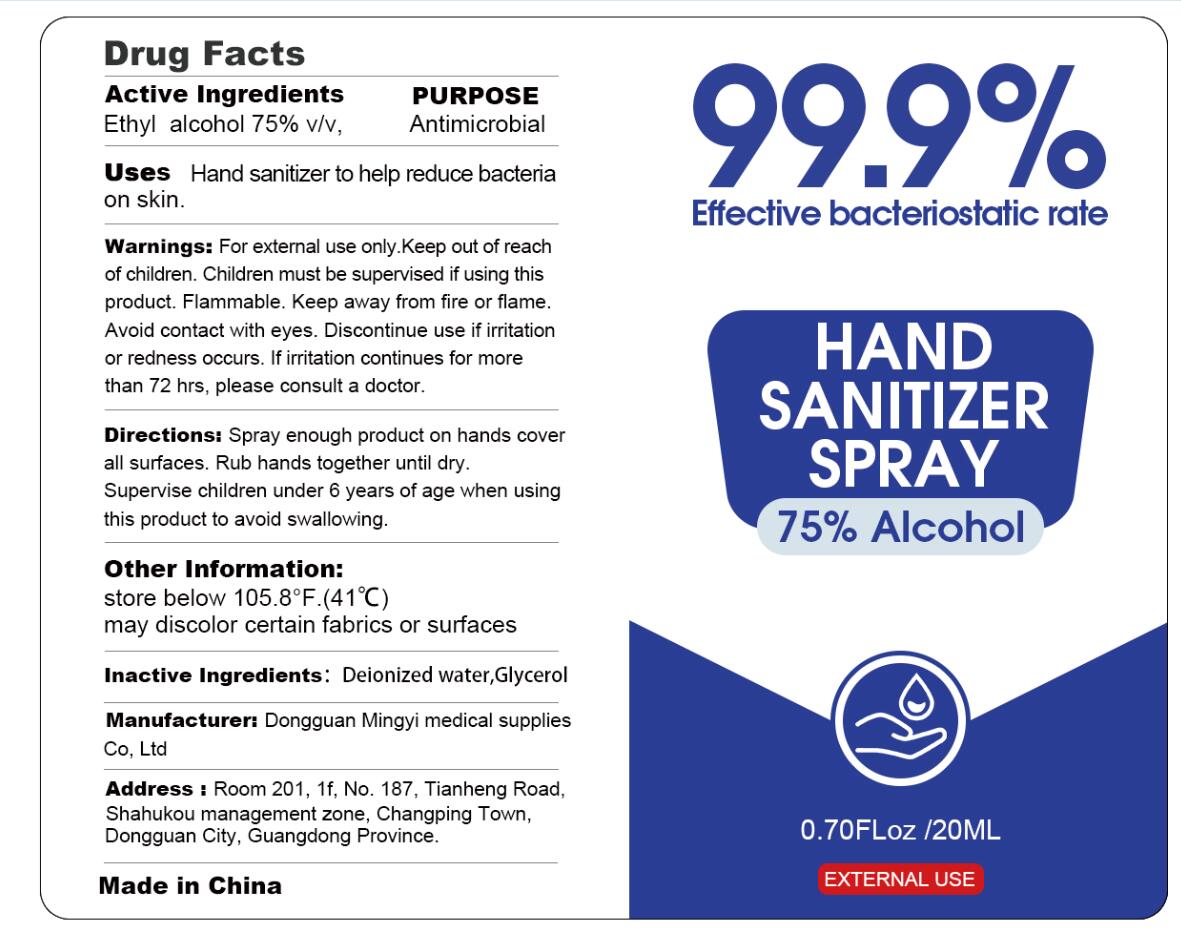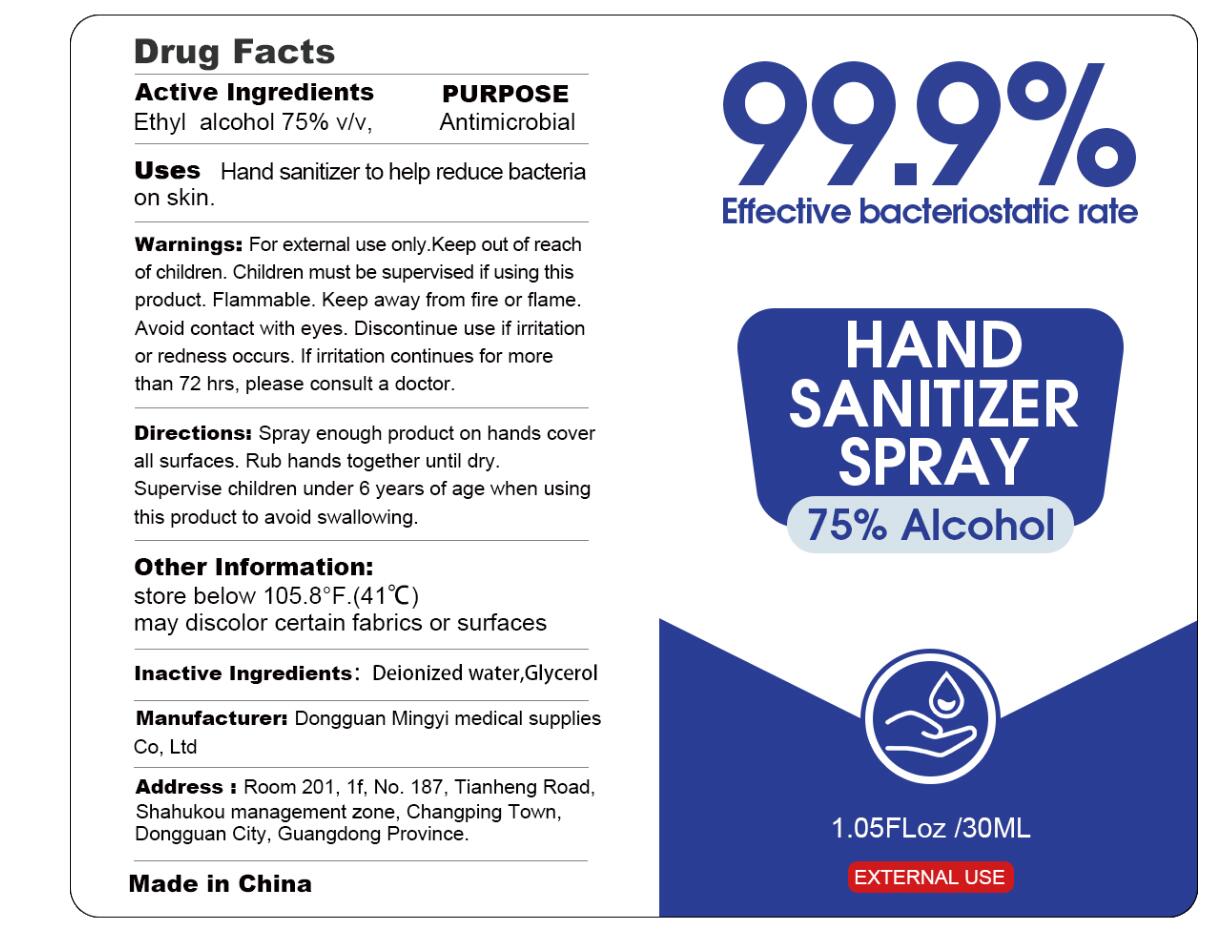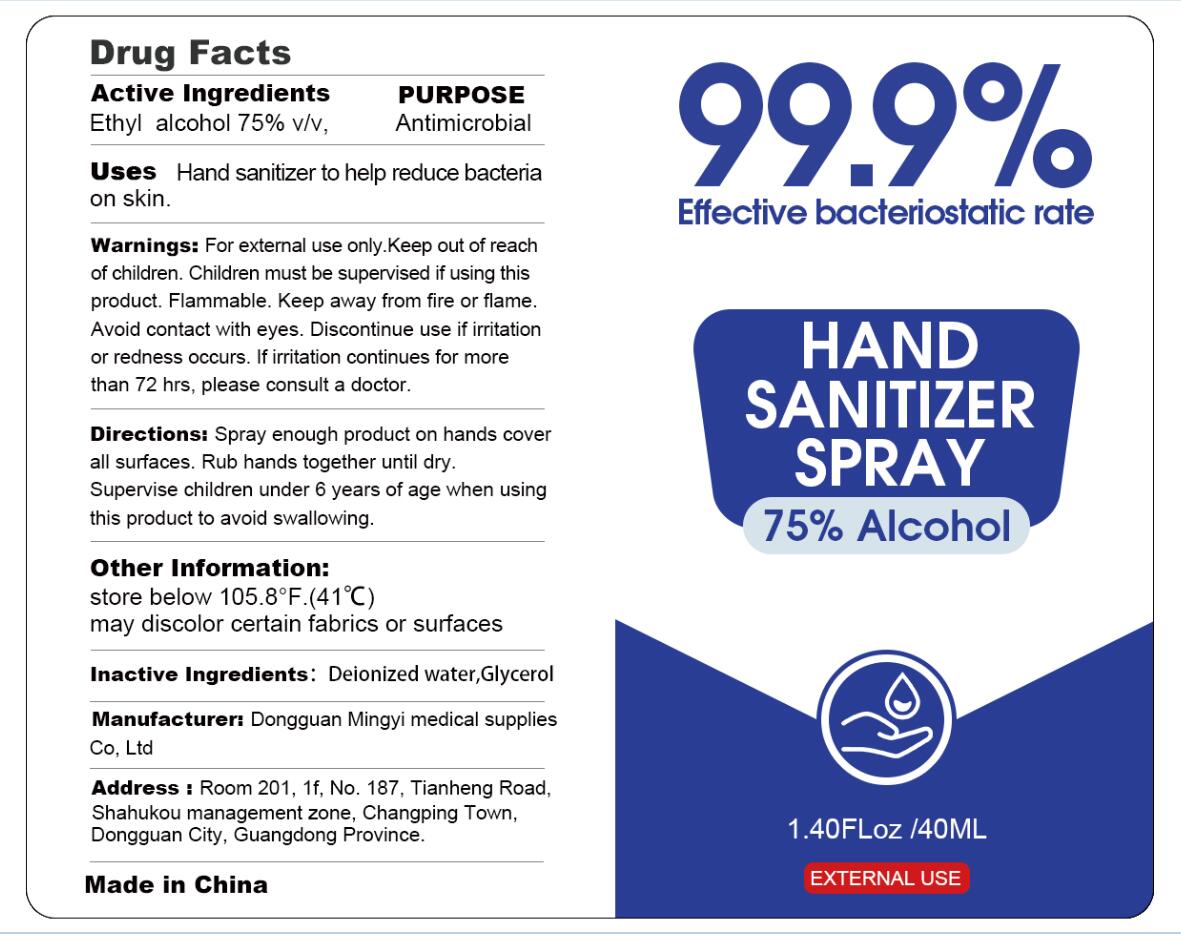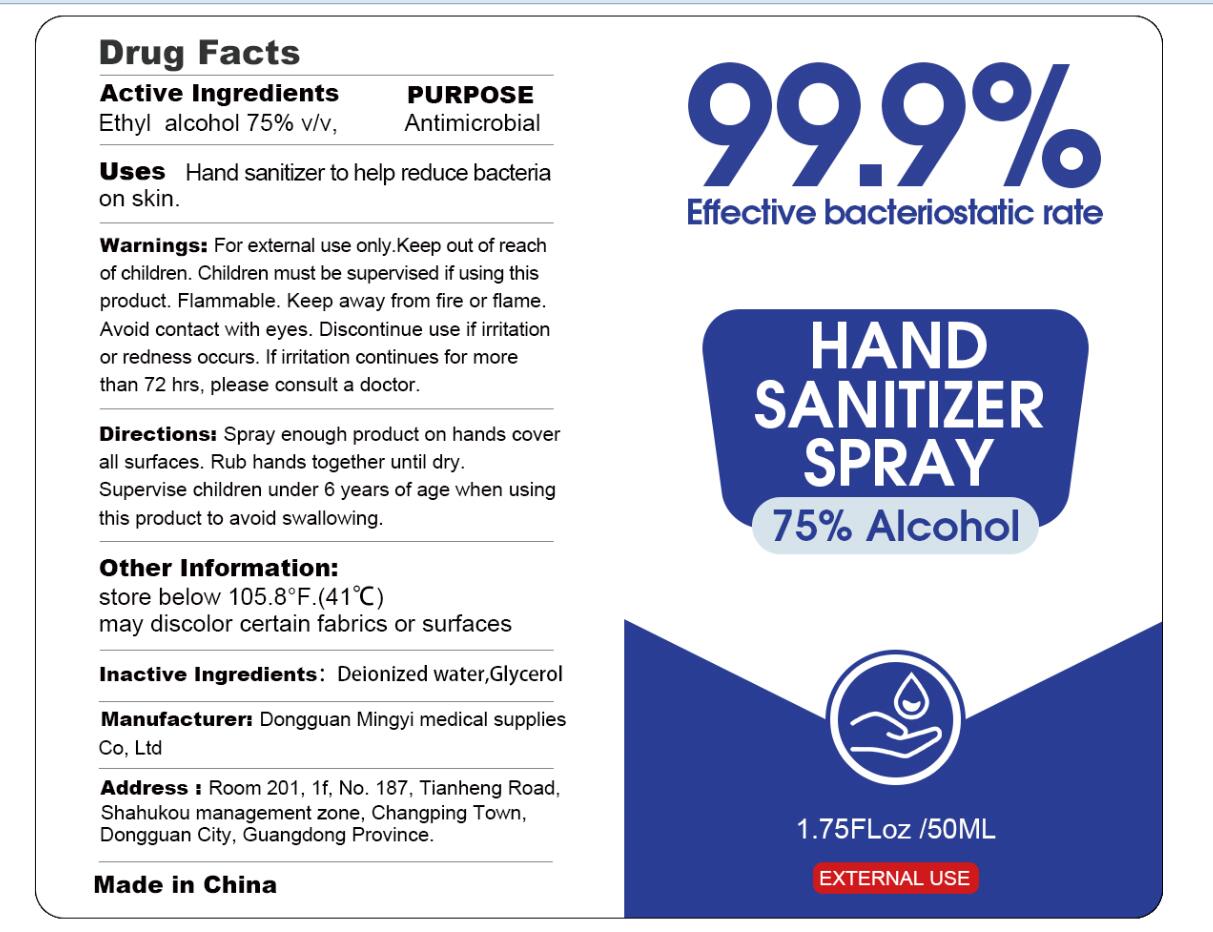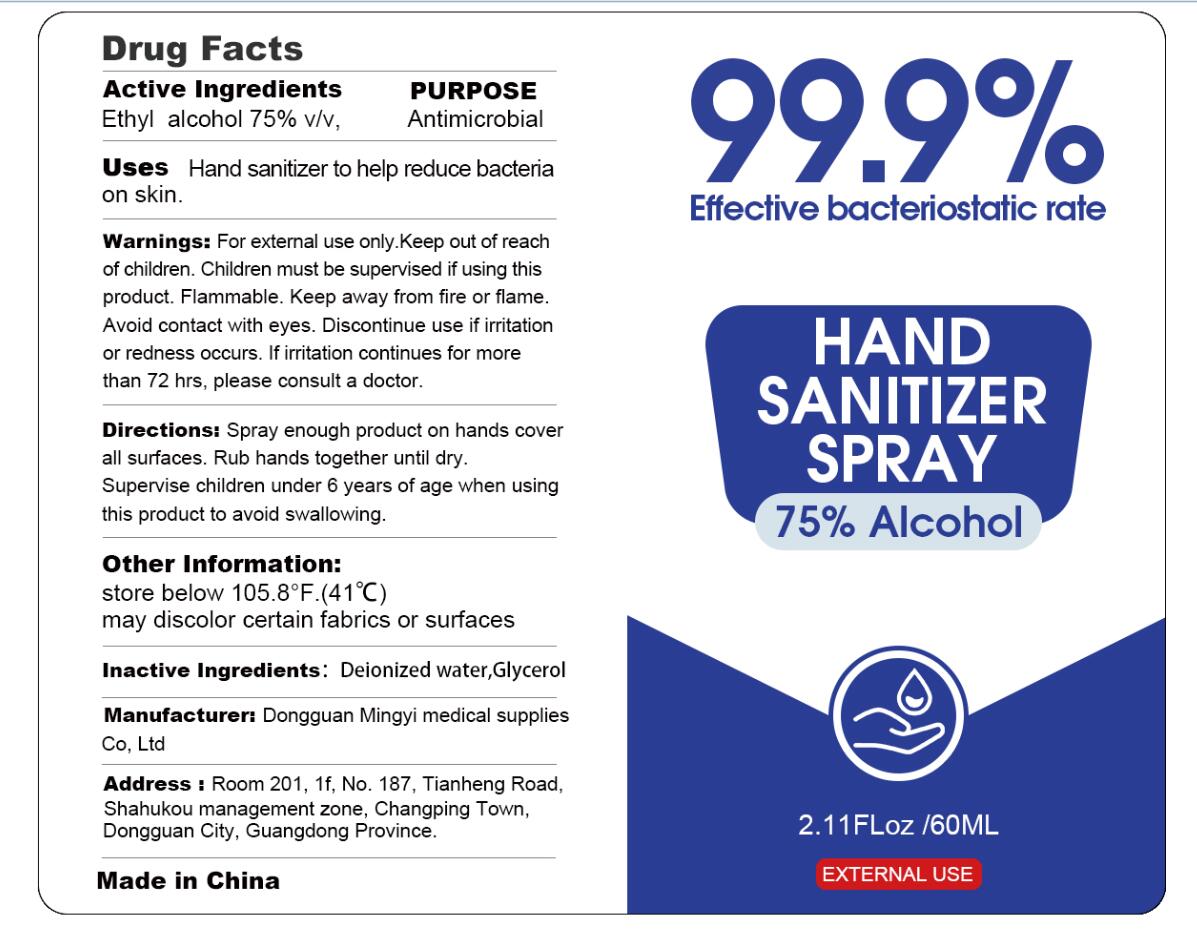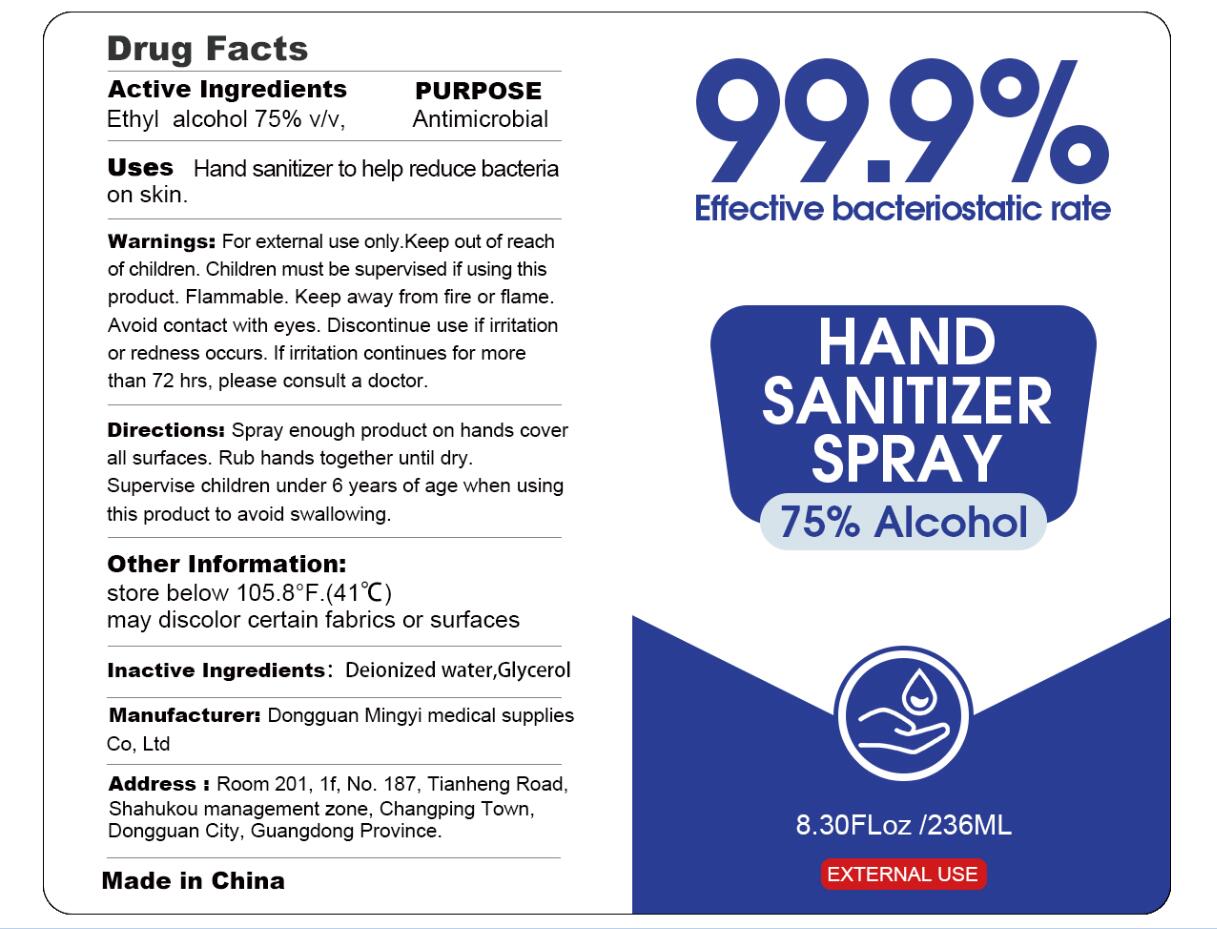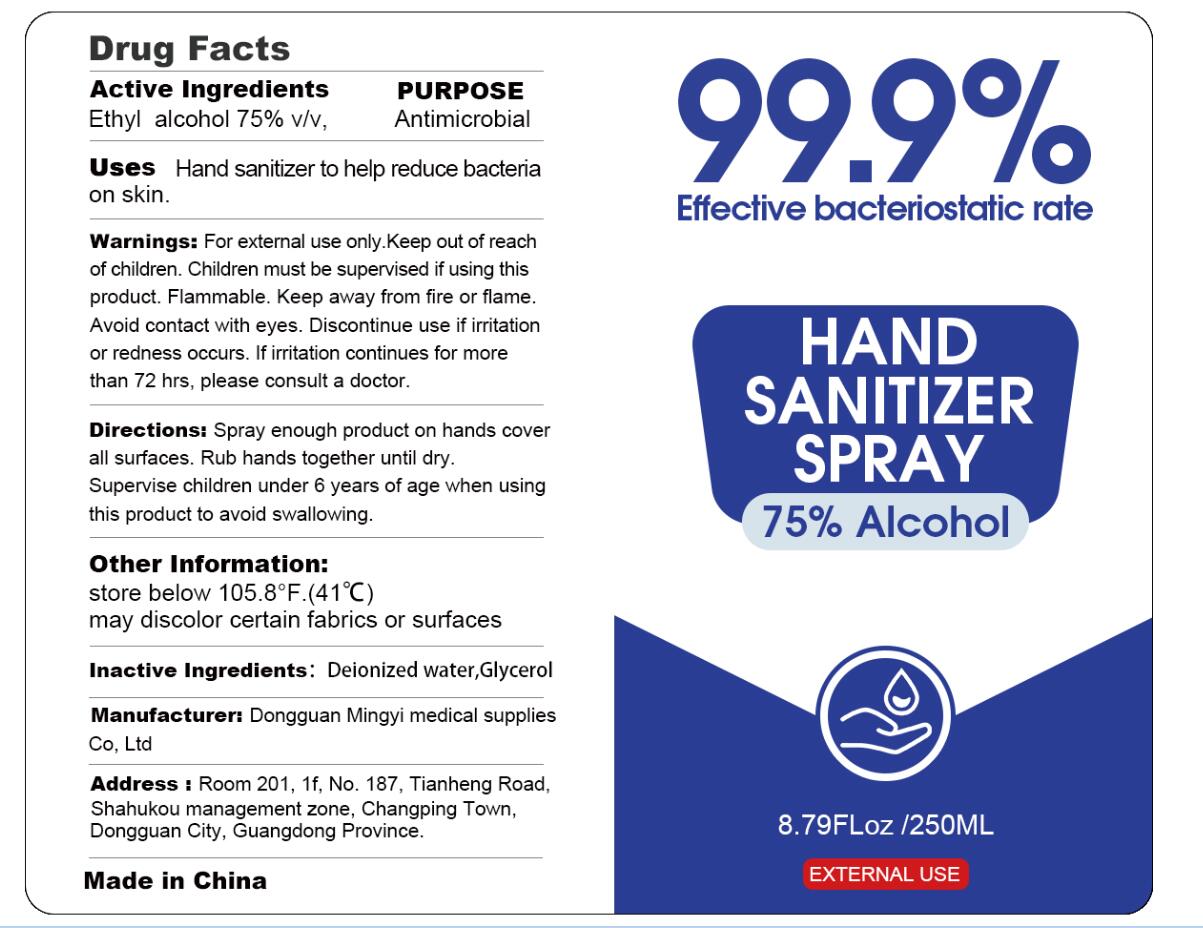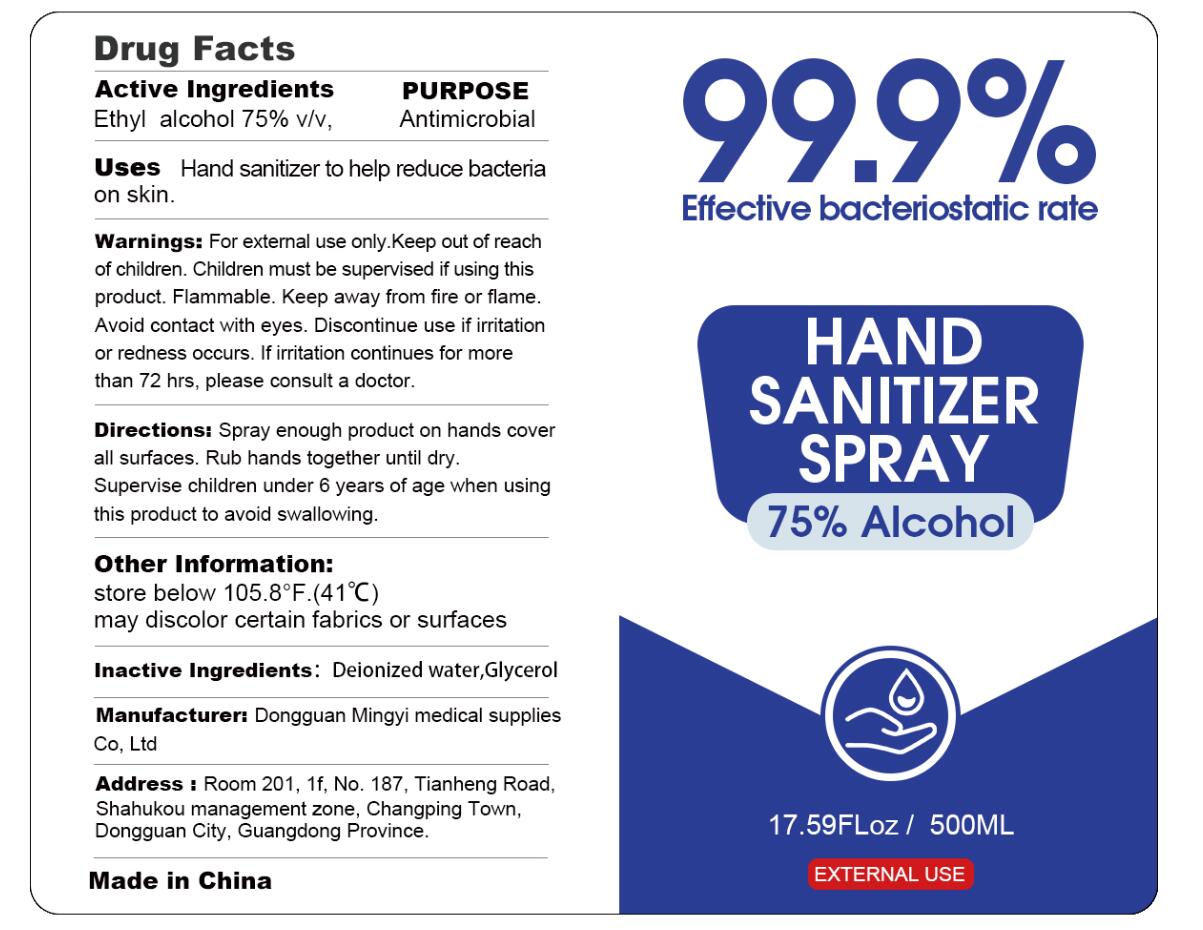 DRUG LABEL: HAND SANITIZER
NDC: 74046-004 | Form: SPRAY
Manufacturer: Dongguan Mingyi Medical Products  Co., Ltd.
Category: otc | Type: HUMAN OTC DRUG LABEL
Date: 20220115

ACTIVE INGREDIENTS: ALCOHOL 75 mL/100 mL
INACTIVE INGREDIENTS: WATER; GLYCERIN

74046-004
HAND SANITIZER SPRAY

Active Ingredients

Ethyl Alcohol 75%

Purpose

Antimicrobial

Uses

Hand sanitizer to help reduce bacteria on skin.

Warnings

For external use only. Keep out of reach of children. Children must be supervised if using this product. Flammable. Keep away from fire or flame .Avoid contact with eyes. Discontinue use if irritation or redness occurs , If irritation continues for more than 72 hrs , please consult a doctor.

Directions

Spray enough product on hands cover all surfaces. Rub hands together until dry. Supervise children under 6 years of age when using this product to avoid swallowing.

Other Information

store below 105. 8℉ (41℃)

may discolor certain fabrics or surfaces

Inactive Ingredients

Deionized water , Glycerol